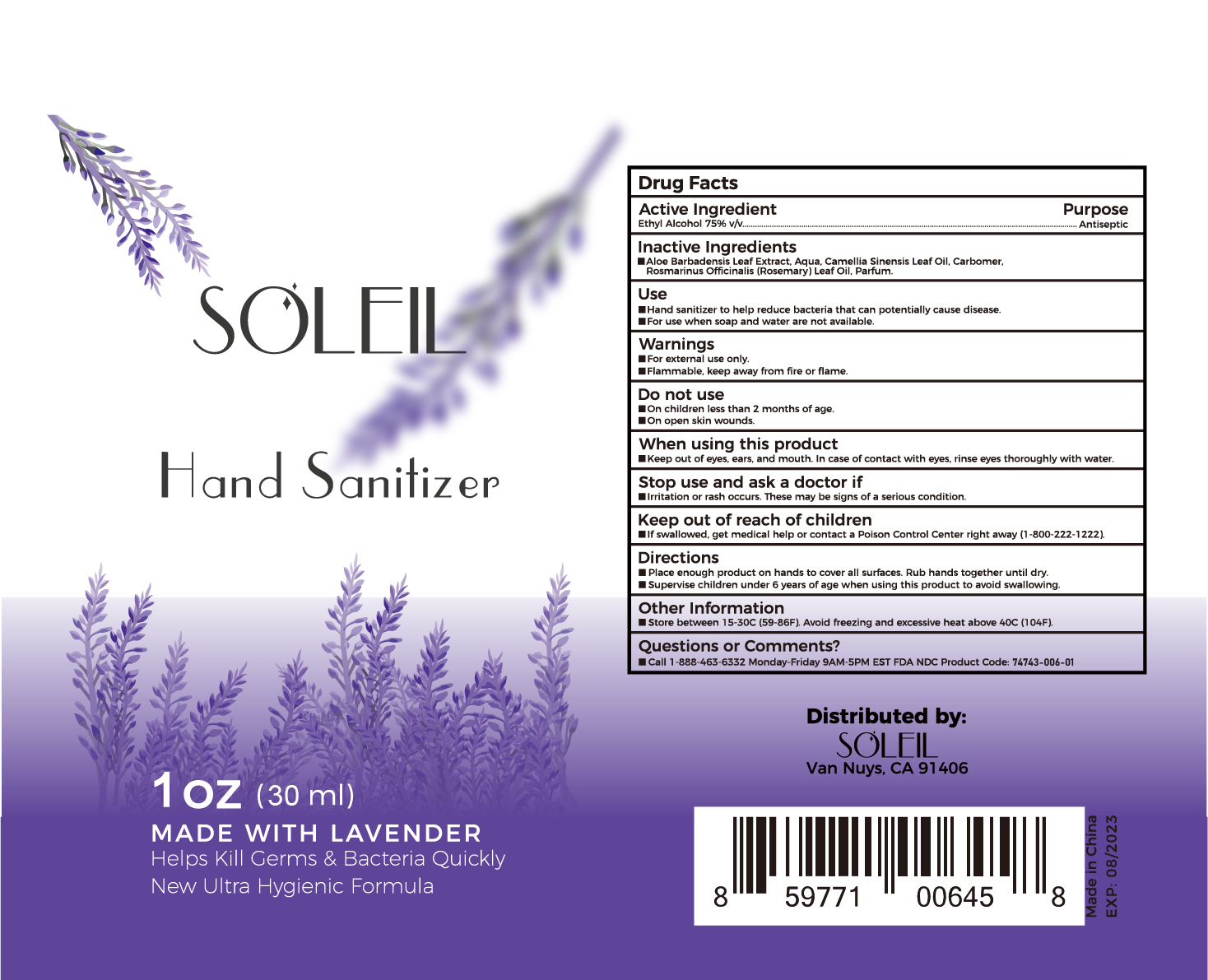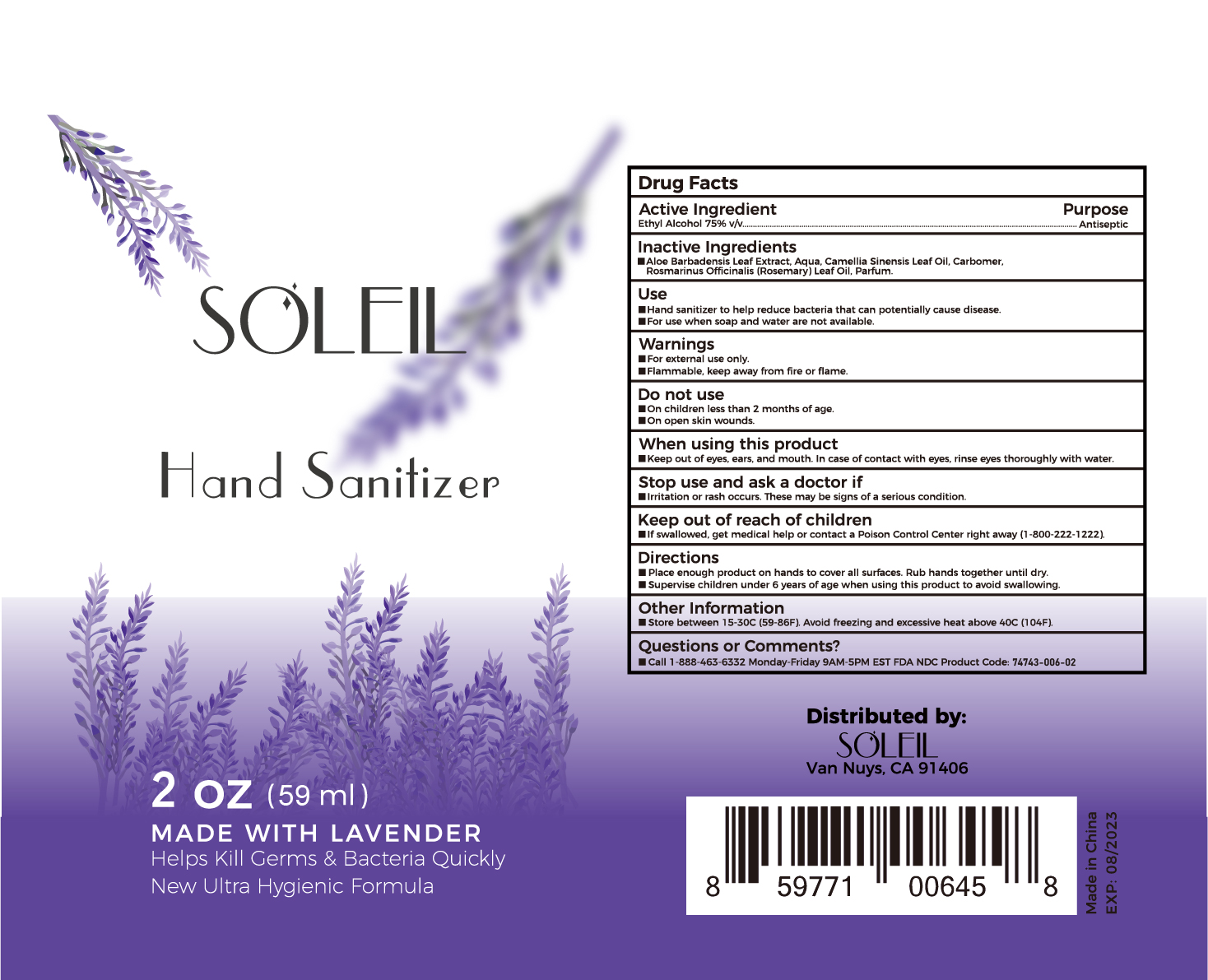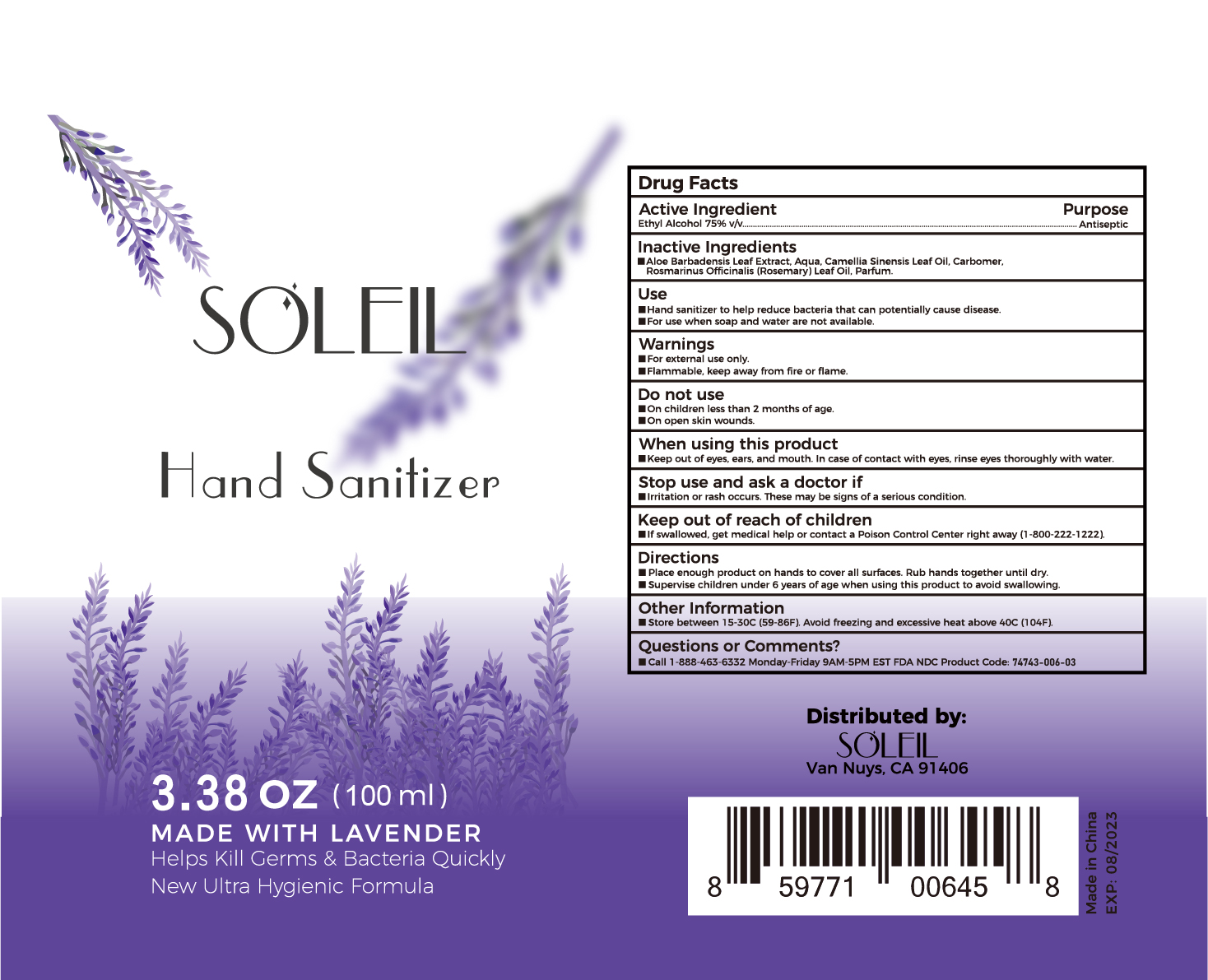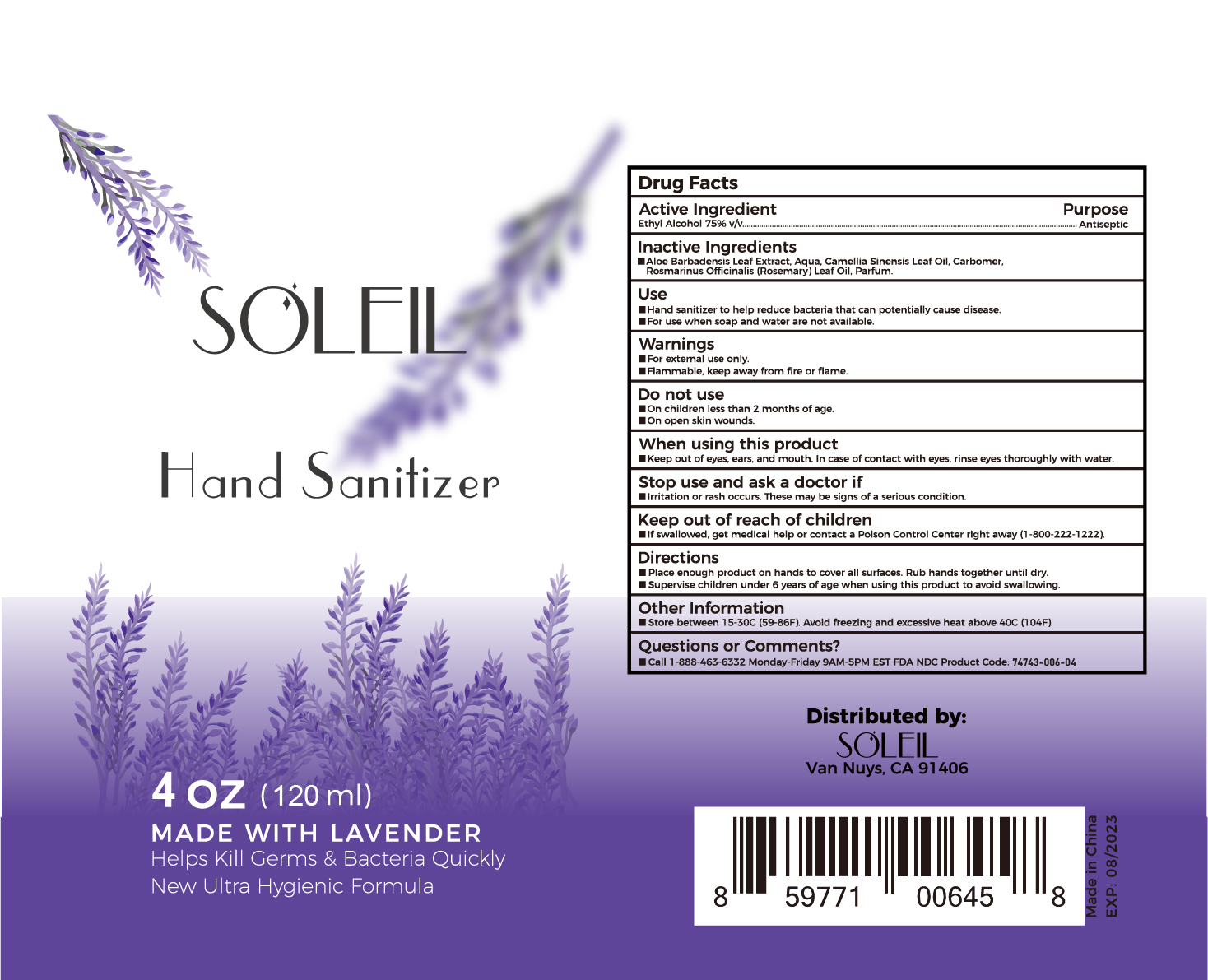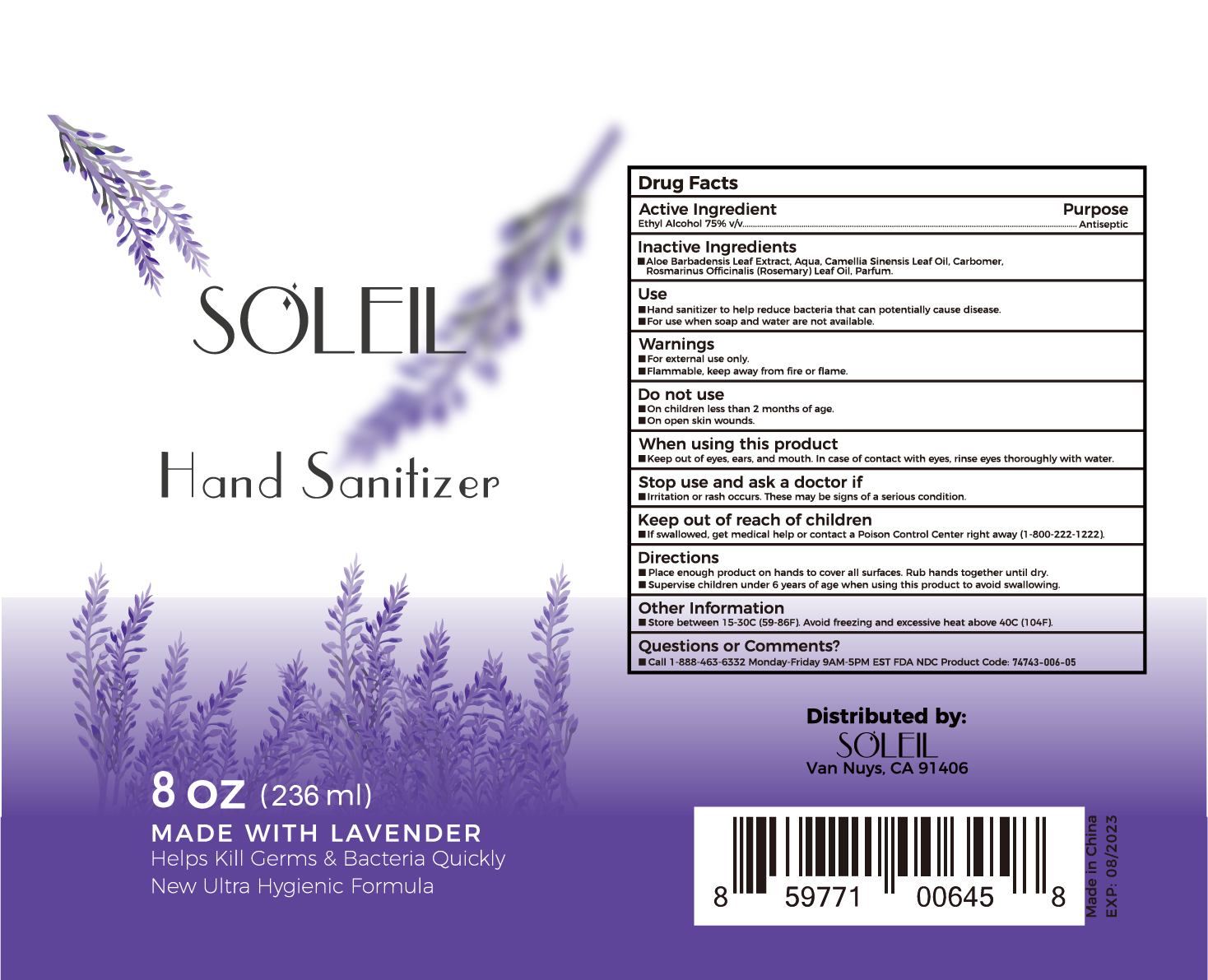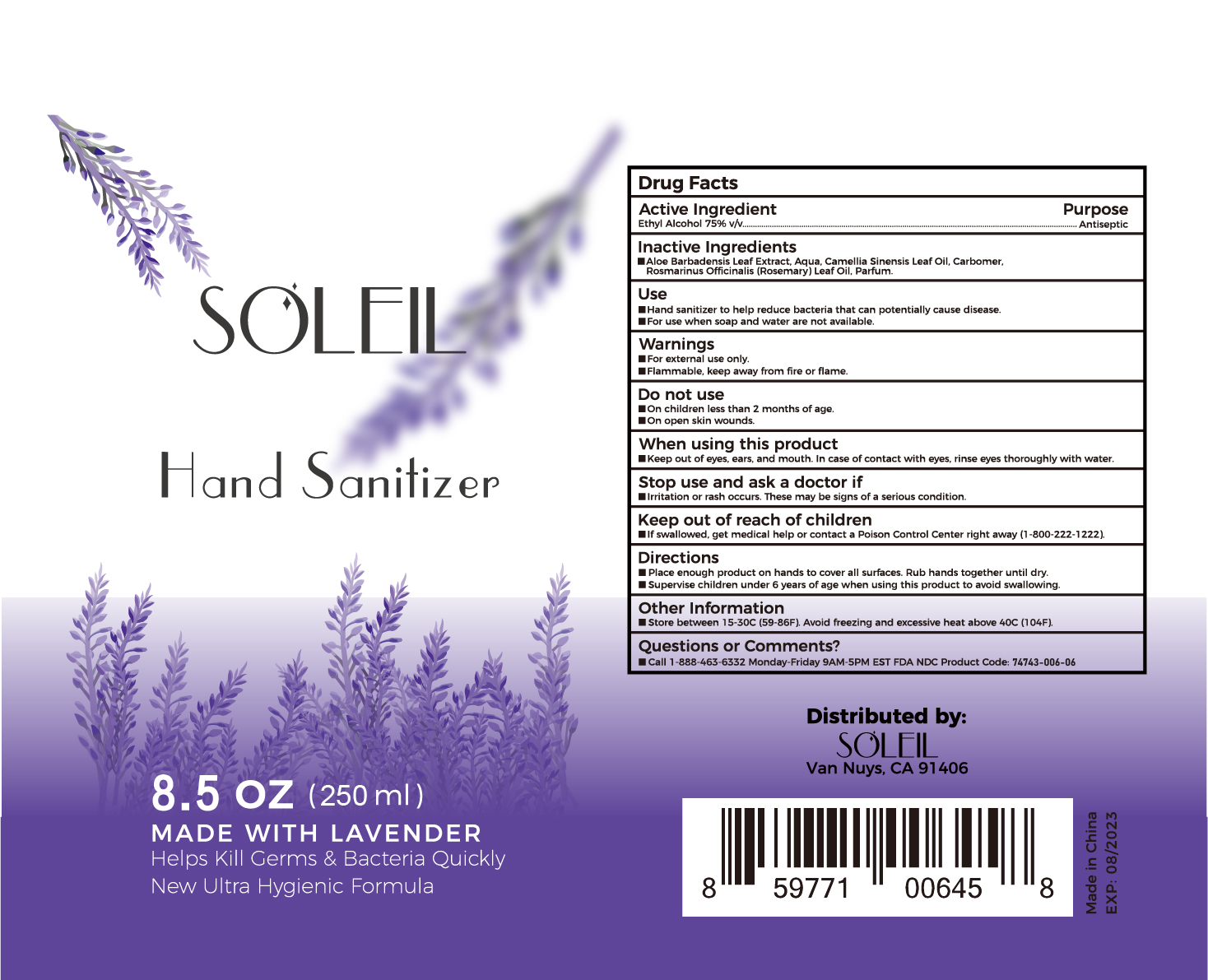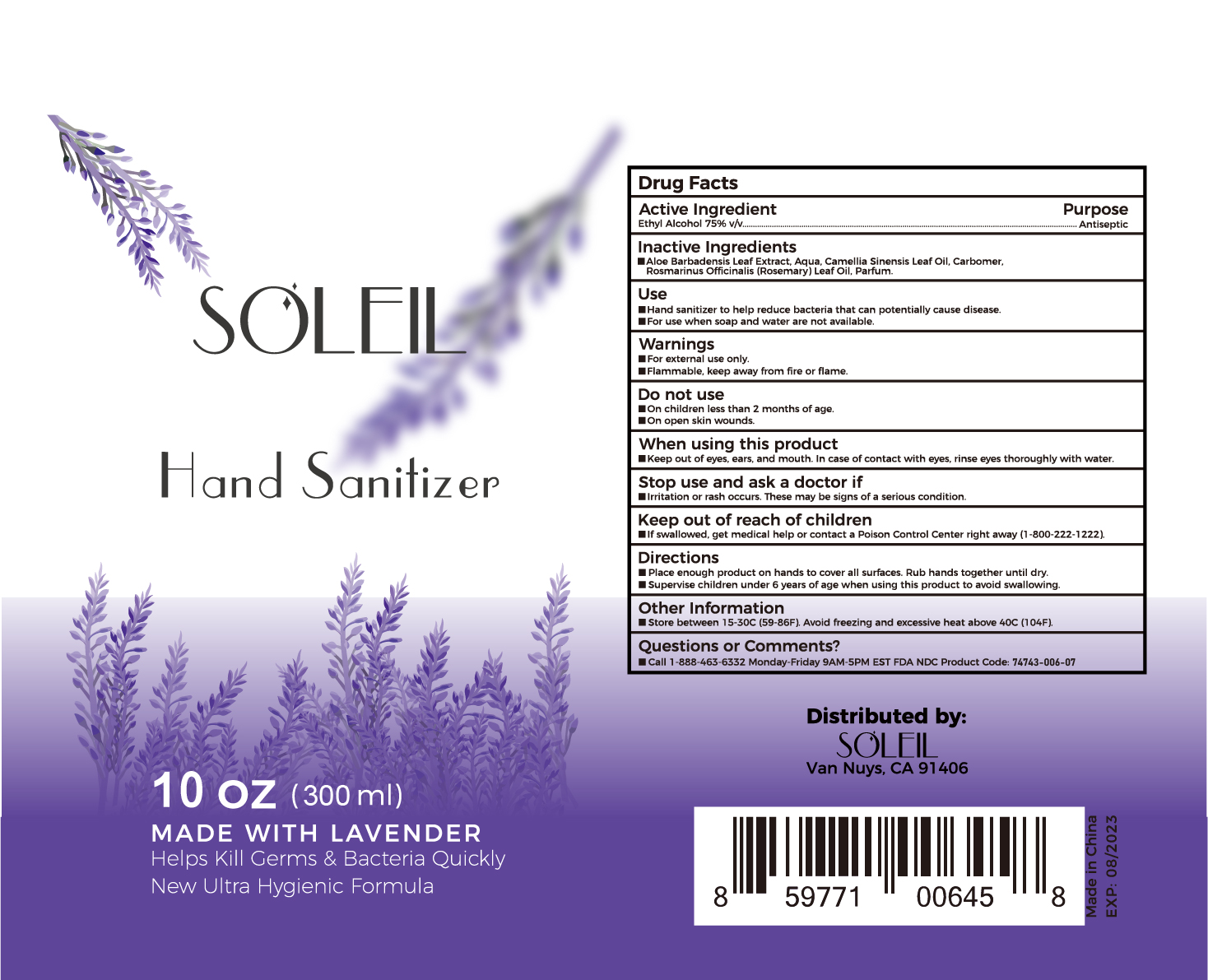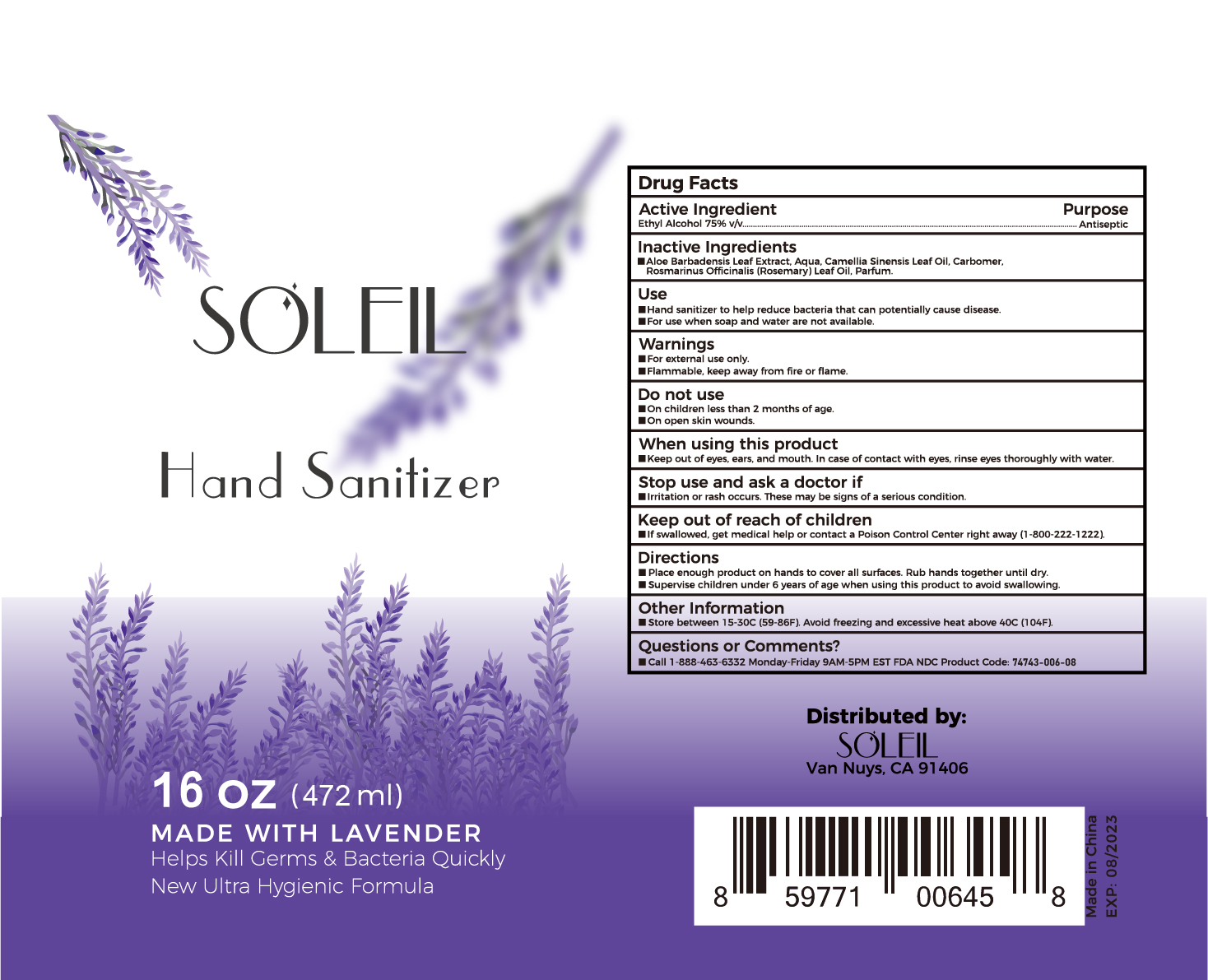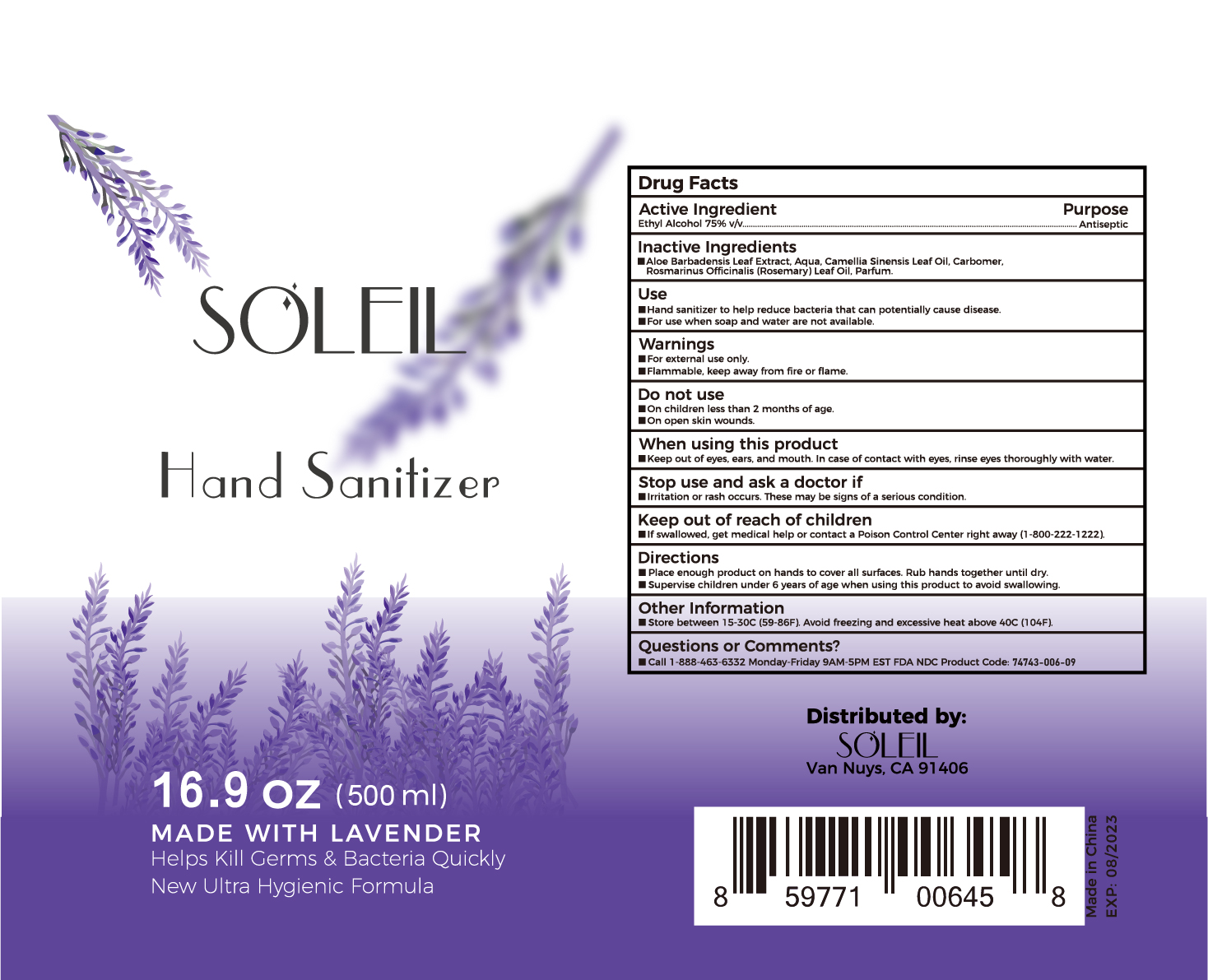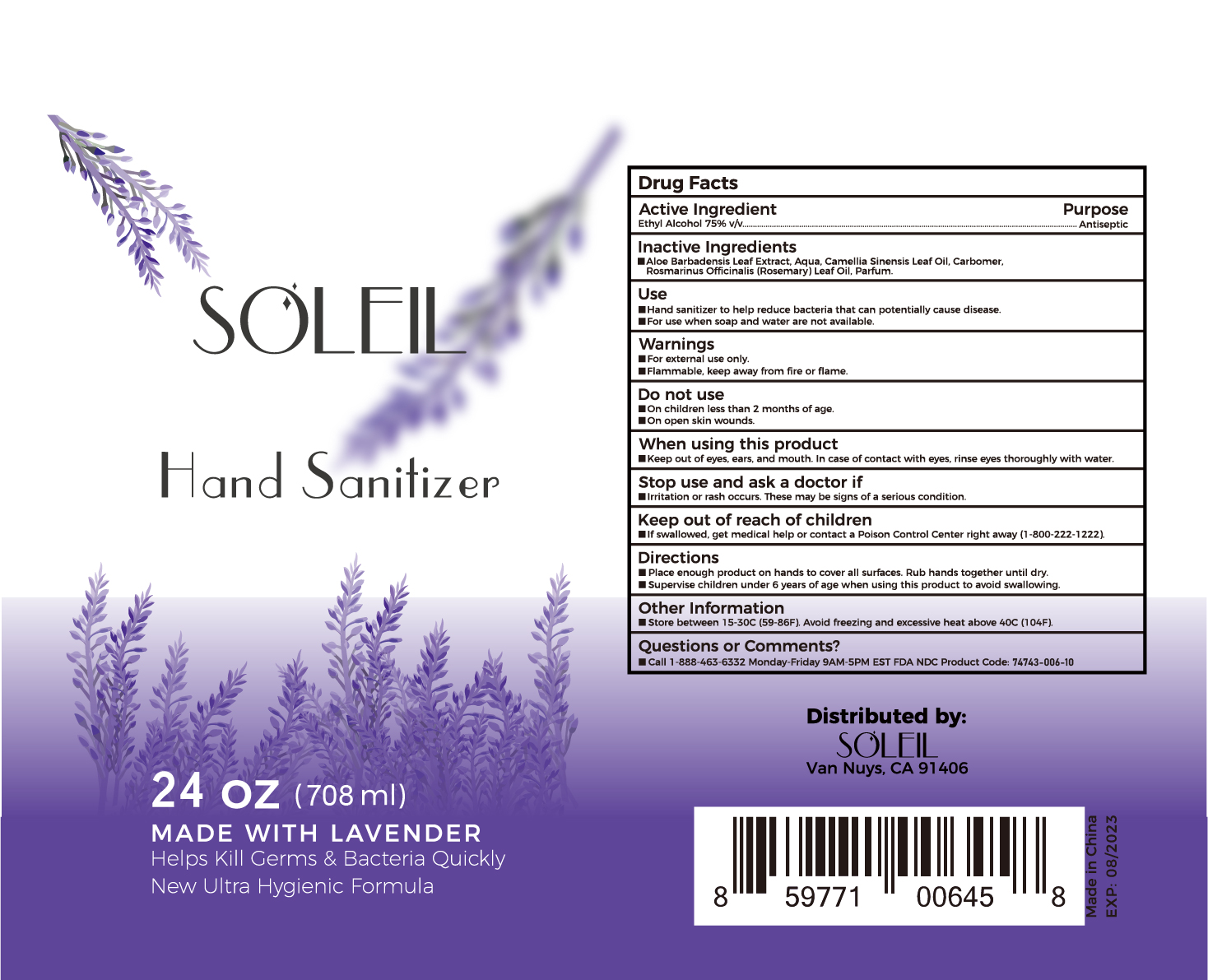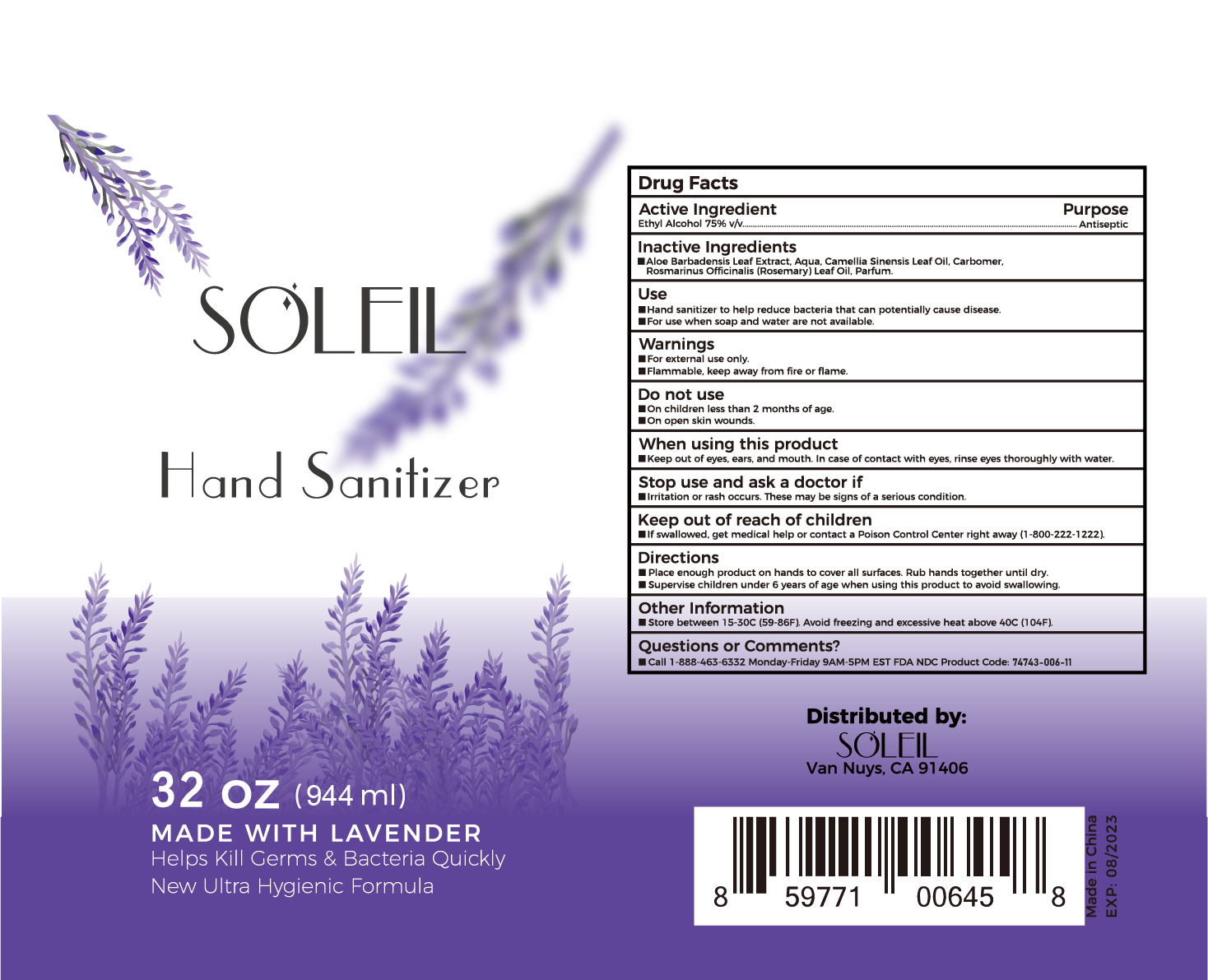 DRUG LABEL: Hand Sanitizer
NDC: 74743-006 | Form: GEL
Manufacturer: Guangzhou Joy Claire Biological Technology   Co., Ltd
Category: otc | Type: HUMAN OTC DRUG LABEL
Date: 20200827

ACTIVE INGREDIENTS: ALCOHOL 75 mL/100 mL
INACTIVE INGREDIENTS: ROSEMARY; CAMELLIA SINENSIS SEED; CARBOMER HOMOPOLYMER, UNSPECIFIED TYPE; METHYL BENZOATE; WATER; ALOE

74743-006
Hand Sanitizer

Active Ingredient(s)

Ethyl Alcohol 75%v/v

Purpose

Antiseptic

Use

Hand sanitizer to help reduce bacteria that can potentially cause disease
For use when soap and water are not available

Warnings

For external use only.
Flammable, keep away from fire or flame

Keep out of reach of children If swallowed, get medical help or contact a poison Control Center right away(1-800-222-1222)

Do not use

On children less than 2 months of age
On open skin wounds

WHEN USING

Keep out of eyes, ears, and mouth In case of contact with eyes, rinse eyes thoroughly with water.

Other information

Store between 15-30C(59-86F) Avoid freezing and excessive heat above 40C (104F)

Stop use and ask a doctor if rritation or rash occurs. These may be signs of a serious condition

Directions

Place enough product on hands to cover all surfaces. Rub hands together until dry
Supervise children under 6 years of age when using this product to avoid swallowing

Inactive ingredients

Aloe Barbadensis Leaf Extract, Aqua, Camellia Sinensis Leaf Oil, Carbomer, Rosmarinus Officinalis(Rosemary)Leaf oil, Parfum